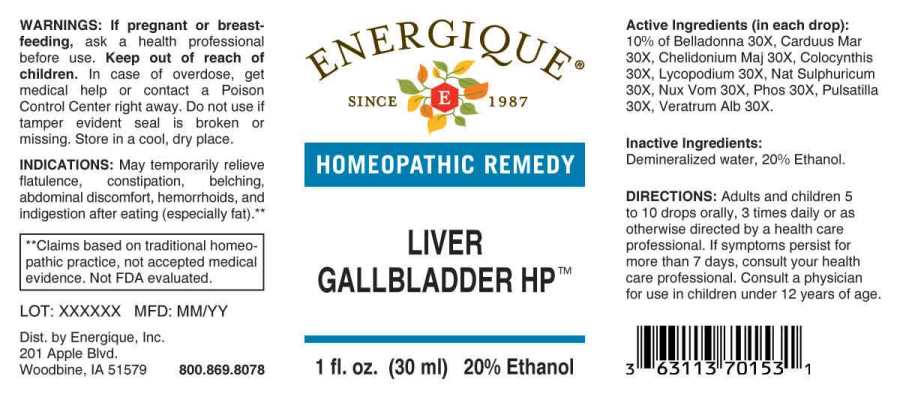 DRUG LABEL: Liver Gallbladder
NDC: 44911-0506 | Form: LIQUID
Manufacturer: Energique, Inc.
Category: homeopathic | Type: HUMAN OTC DRUG LABEL
Date: 20230807

ACTIVE INGREDIENTS: ATROPA BELLADONNA 30 [hp_X]/1 mL; SILYBUM MARIANUM SEED 30 [hp_X]/1 mL; CHELIDONIUM MAJUS 30 [hp_X]/1 mL; CITRULLUS COLOCYNTHIS FRUIT PULP 30 [hp_X]/1 mL; LYCOPODIUM CLAVATUM SPORE 30 [hp_X]/1 mL; SODIUM SULFATE 30 [hp_X]/1 mL; STRYCHNOS NUX-VOMICA SEED 30 [hp_X]/1 mL; PHOSPHORUS 30 [hp_X]/1 mL; ANEMONE PRATENSIS 30 [hp_X]/1 mL; VERATRUM ALBUM ROOT 30 [hp_X]/1 mL
INACTIVE INGREDIENTS: WATER; ALCOHOL

Drug Facts:

ACTIVE INGREDIENTS:

(in each drop): 10% of Belladonna 30X, Carduus Marianus 30X, Chelidonium Majus 30X, Colocynthis 30X, Lycopodium Clavatum 30X, Natrum Sulphuricum 30X, Nux Vomica 30X, Phosphorus 30X, Pulsatilla 30X, Veratrum Album 30X.

INDICATIONS:

May temporarily relieve flatulence, constipation, belching, abdominal discomfort, hemorrhoids and indigestion after eating (especially fat).**

**Claims based on traditional homeopathic practice, not accepted medical evidence. Not FDA evaluated.

WARNINGS:

If pregnant or breast-feeding, ask a health professional before use.

Keep out of reach of children. In case of overdose, get medical help or contact a Poison Control Center right away.

Do not use if tamper evident seal is broken or missing.

Store in a cool, dry place.

Keep out of reach of children. In case of overdose, get medical help or contact a Poison Control Center right away.

DIRECTIONS:

Adults and children 5 to 10 drops orally, 3 times daily or as otherwise directed by a health care professional. If symptoms persist for more than 7 days, consult your health care professional. Consult a physician for use in children under 12 years of age.

INDICATIONS:

May temporarily relieve flatulence, constipation, belching, abdominal discomfort, hemorrhoids and indigestion after eating (especially fat).**

**Claims based on traditional homeopathic practice, not accepted medical evidence. Not FDA evaluated.

INACTIVE INGREDIENTS:

Demineralized water, 20% Ethanol.

QUESTIONS:

Dist. by Energique, Inc.

201 Apple Blvd

Woodbine, IA 51579 800.869.8078

PACKAGE LABEL DISPLAY:

ENERGIQUE

SINCE 1987

HOMEOPATHIC REMEDY

LIVER

GALLBLADDER HP

1 fl. oz. (30 ml)